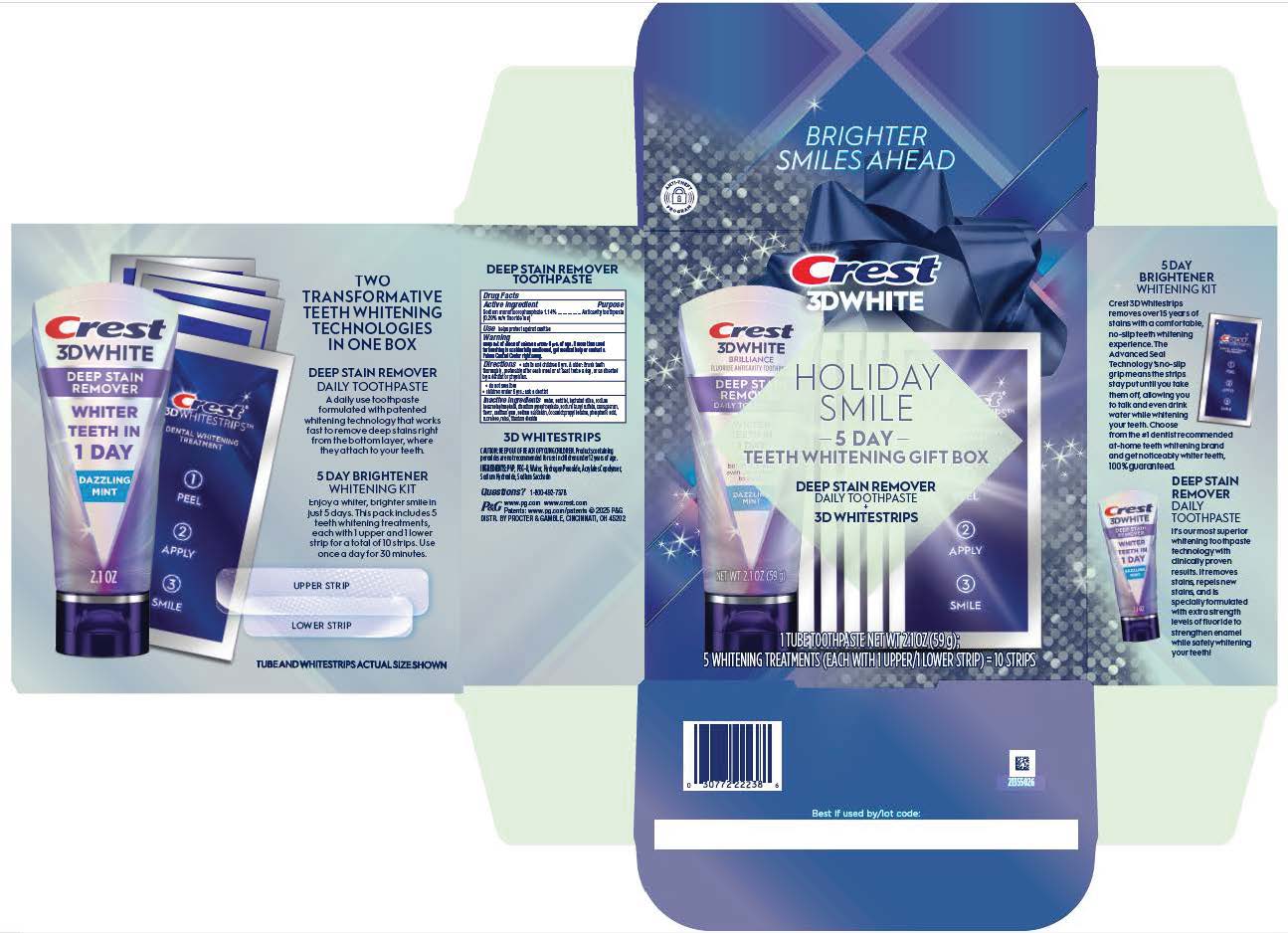 DRUG LABEL: Crest 3D White
NDC: 84126-617 | Form: KIT | Route: ORAL
Manufacturer: The Procter & Gamble Manufacturing Company
Category: otc | Type: HUMAN OTC DRUG LABEL
Date: 20250814

ACTIVE INGREDIENTS: SODIUM MONOFLUOROPHOSPHATE 2 mg/1 g
INACTIVE INGREDIENTS: SODIUM HEXAMETAPHOSPHATE; SODIUM LAURYL SULFATE; SODIUM SACCHARIN; PHOSPHORIC ACID; MICA; HYDRATED SILICA; SORBITOL; WATER; DISODIUM PYROPHOSPHATE; CARRAGEENAN; SUCRALOSE; XANTHAN GUM; COCAMIDOPROPYL BETAINE; TITANIUM DIOXIDE

Crest 3D White Holiday Smile Deep Stain Remover + Whitestrips

Drug Facts

Sodium monofluorophosphate 1.14%

(0.20% w/v fluoride ion)

Purpose

Anticavity toothpaste

Use

helps protect against cavities

Warning

Keep out of reach of children under 6 yrs. of age. If more than used for brushing is accidentally swallowed, get medical help or contact Poison Control Center right away.

Directions

- adults and children 6 yrs. & older: Brush teeth
  thoroughly, preferably after each meal or at least twice a day, or as directed
  by a dentist or physician.
  • do not swallow
  • children under 6 yrs.: ask a dentist

Inactive ingredients

water, sorbitol, hydrated silica, sodium hexametaphosphate, disodium
pyrophosphate, sodium lauryl sulfate, carrageenan, flavor, xanthan gum, sodium saccharin,
cocamidopropyl betaine, phosphoric acid, sucralose, mica, titanium dioxide

Questions?

1-800-492-7378

DISTR. BY PROCTER & GAMBLE, CINCINNATI, OH 45202

Crest 3D White Brilliance 2.1oz Tube of Toothpaste and 5 Whitening Treatments

Crest

3DWHITE

HOLIDAY

SMILE

5 DAY

TEETH WHITENING GIFT BOX

DEEP STAIN REMOVER

DAILY TOOTHPASTE

+

3D WHITESTRIPS

1 TUBE TOOTHPASTE NET WT 2.1OZ (59g);

5 WHITENING TREATMENTS (EACH WITH 1 UPPER/1 LOWER STRIP) = 10 STRIPS